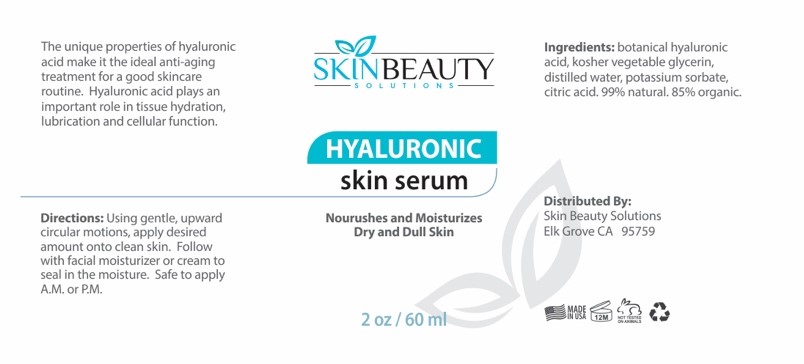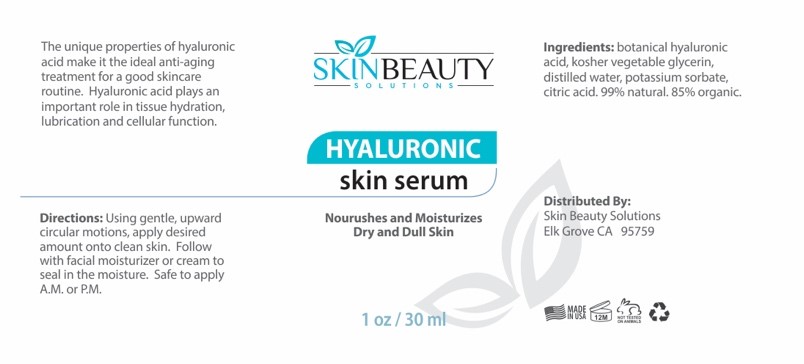 DRUG LABEL: Hyaluronic Acid Serum with Dropper
NDC: 84785-0051 | Form: SOLUTION
Manufacturer: Gazebo Wellness SKIN LLC
Category: otc | Type: HUMAN OTC DRUG LABEL
Date: 20241218

ACTIVE INGREDIENTS: GLYCERIN 3 mg/30 mL; HYALURONIC ACID 1 mg/30 mL
INACTIVE INGREDIENTS: WATER; POTASSIUM SORBATE; CITRIC ACID ACETATE

DOSAGE AND ADMINISTRATION

Directions: Using gentle, upward circular motions, apply desired amount onto clean skin. Follow with facial moisturizer or cream to seal in the moisture. Safe to apply A.M. or PM.

WARNINGS

The unique properties of hyaluronic acid make it the ideal anti-aging treatment for a good skincare routine.

Inactive Ingredients: Distilled Water, Potassium Sorbate, Citric Acid

ACTIVE INGREDIENT

Active Ingredients: Botanical Hyaluronic Acid, Kosher Vegetable Glycerin

INDICATIONS AND USAGE

The unique properties of hyaluronic acid make it the ideal anti-aging treatment for a good skincare routine. Hyaluronic acid plays an important role in tissue hydration, lubrication and cellular function.

keep out of reach of children

PURPOSE

The unique properties of hyaluronic acid make it the ideal anti-aging treatment for a good skincare routine. Hyaluronic acid plays an important role in tissue hydration, lubrication and cellular function.

HYALURONIC skin serum
Nourushes and Moisturizes Dry and Dull Skin
Distributed By:
Skin Beauty Solutions Elk Grove CA 95759

PACKAGE LABEL

Content of Labeling